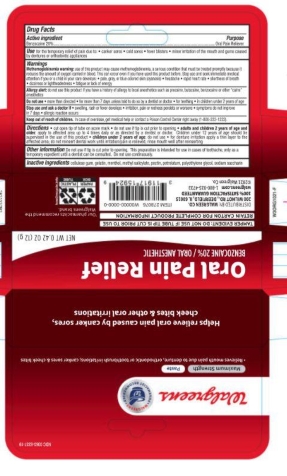 DRUG LABEL: Walgreens
NDC: 0363-5337 | Form: PASTE, DENTIFRICE
Manufacturer: Walgreens
Category: otc | Type: HUMAN OTC DRUG LABEL
Date: 20251121

ACTIVE INGREDIENTS: BENZOCAINE 20 g/100 g
INACTIVE INGREDIENTS: MENTHOL; PETROLATUM; GELATIN; POLYETHYLENE GLYCOL, UNSPECIFIED; SACCHARIN; METHYL SALICYLATE; PECTIN; CARBOXYMETHYLCELLULOSE SODIUM, UNSPECIFIED FORM

5820337 Walgreens Max Str Oral Anesthetic Paste

Drug Facts

Active ingredient

Benzocaine 20%

Purpose

Oral pain reliever

INDICATIONS AND USAGE

Use for the temporary relief of pain due to:

- canker sores
- cold sores
- fever blisters
- minor irritation of the mouth and gums
- minor irritation of the mouth and gums caused by dentures or orthodontic appliances

Warnings

Allergy alert: do not use this product if you have a history of allergy to local anesthetics such as procaine, butacaine, benzocaine or other “caine” anesthetics.

When using this product

- avoid contact with eyes
- do not use more than directed
- do not use for more than 7 days unless told to do so by a dentist or doctor.

Stop use and ask a doctor if

- sore mouth symptoms do not improve in 7 days
- swelling, rash or fever develops
- irritation, pain or redness persists or worsens

Keep out of reach of children. In case of overdose, get medical help or contact a Poison Control Center right away.

Directions

- cut open tip of tube on score mark
- adults and children 2 years of age and older: apply to the affected area up to 4 times daily or as directed by a dentist or doctor. Children under 12 years of age should be supervised in the use of this product
- children under 2 years of age: ask a dentist or doctor
- for denture irritation apply a thin layer to the affected area; do not reinsert dental work until irritation/pain is relieved; rinse mouth well after reinserting

Other information Do not use if tip is cut prior to opening. This preparation is intended for use in cases of toothache, only as a

temporary expedient until a dentist can be consulted. Do not use continuously.

INACTIVE INGREDIENT

Inactive ingredients Cellulose Gum, Gelatin, Menthol, Methyl Salicylate, Pectin, Petrolatum, Polyethylene Glycol, Sodium Saccharin.

Questions or comments? 1-877-777-2743

DISTRIBUTED BY: WALGREEN CO.

200 WILMOT RD., DEERFIELD, IL 60015

100% SATISFACTION GUARANTEED

walgreens.com

MADE IN U.S.A.